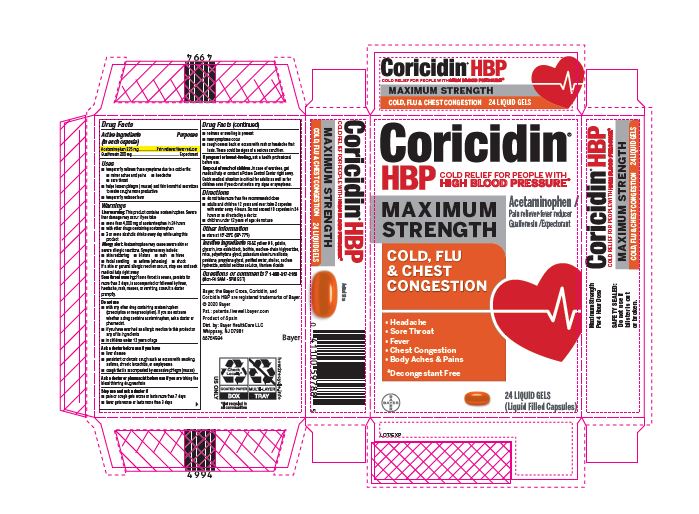 DRUG LABEL: Coricidin HBP Maximum Strength Cold Flu And Chest Congestion
NDC: 11523-0094 | Form: CAPSULE, GELATIN COATED
Manufacturer: Bayer HealthCare LLC.
Category: otc | Type: HUMAN OTC DRUG LABEL
Date: 20251204

ACTIVE INGREDIENTS: ACETAMINOPHEN 325 mg/1 1; GUAIFENESIN 200 mg/1 1
INACTIVE INGREDIENTS: WATER; SORBITOL; MICA; LECITHIN, SOYBEAN; SODIUM HYDROXIDE; MEDIUM-CHAIN TRIGLYCERIDES; SHELLAC; FD&C YELLOW NO. 6; SORBITAN; POTASSIUM ALUMINUM DISILICATE; POLYETHYLENE GLYCOL, UNSPECIFIED; POVIDONE; TITANIUM DIOXIDE; FERROSOFERRIC OXIDE; PROPYLENE GLYCOL; GELATIN; GLYCERIN

Coricidin® HBP Maximum Strength Cold, Flu & Chest Congestion Liquid Gels

Drug Facts

ACTIVE INGREDIENT

Active ingredients (in each tablet) | Purpose
Acetaminophen 325 mg | Pain reliever/ fever reducer
Guaifenesin 200 mg | Expectorant

Uses

- temporarily relieves these symptoms due to a cold or flu:
  - minor aches and pains
  - headache
  - sore throat
  - helps loosen phlegm(mucus) and thin bronchial secretions to make coughs more productive
- temporarily reduces fever

Warnings

Liver warning: This product contains acetaminophen. Severe liver damage may occur if you take • more than 4,000 mg of acetaminophen in 24 hours • with other drugs containing acetaminophen • 3 or more alcoholic drinks every day while using this product

Allergy alert: Acetaminophen may cause severe skin or severe allergic reactions. Symptoms may include: • skin reddening • blisters • rash • hives • facial swelling • asthma (wheezing) • shock If a skin or general allergic reaction occurs, stop use and seek medical help right away.

Sore throat warning: If sore throat is severe, persists for more than 2 days, is accompanied or followed by fever, headache, rash, nausea, or vomiting, consult a doctor promptly

Do not use

● with any other drug containing acetaminophen (prescription or nonprescription). If you are not sure whether a drug contains acetaminophen, ask a doctor or pharmacist.

● if you have ever had an allergic reaction to this product or any of its ingredients
● in children under 12 years of age

Ask a doctor before use if you have ● liver disease ● persistent or chronic cough such as occurs with smoking, asthma, chronic bronchitis, or emphysema ● cough that is accompanied by excessive phlegm (mucus)

Ask a doctor or pharmacist before use if you are taking the blood thinning drug warfarin

Stop use and ask a doctor if • pain or cough gets worse or lasts more than 7 days • fever gets worse or lasts more than 3 days • redness or swelling is present • new symptoms occur • cough comes back or occurs with rash or headache that lasts. These could be signs of a serious condition.

PREGNANCY OR BREAST FEEDING

If pregnant or breast-feeding, ask a health professional before use.

Keep out of reach of children. In case of overdose, get medical help or contact a Poison Control Center right away. Quick medical attention is critical for adults as well as for children even if you do not notice any signs or symptoms.

Directions

• do not take more than the recommended dose
• adults and children 12 years and over: take 2 capsules with water every 4 hours. Do not
exceed 10 capsules in 24 hours or as directed by a doctor.
• children under 12 years of age: do not use

Other information

● store at 15º-25ºC (59º-77ºF)

Inactive ingredients

FD&C yellow # 6, gelatin, glycerin, iron oxide black, lecithin, medium-chain triglycerides, mica, polyethylene glycol, potassium aluminum silicate, povidone, propylene glycol,purified water, shellac, sodium hydroxide, sorbitol sorbitan solution,titanium dioxide

?

Questions or comments? 1-800-317-2165 (Mon-Fri 9AM -5PM EST)

PRINCIPAL DISPLAY PANEL - 24 Liquid Gels

Coricidin®

HIGH BLOOD PRESSURE

Acetaminophen - Pain Reliever/Fever Reducer

Guaifenesin - Expectorant

24 Liquid Gels